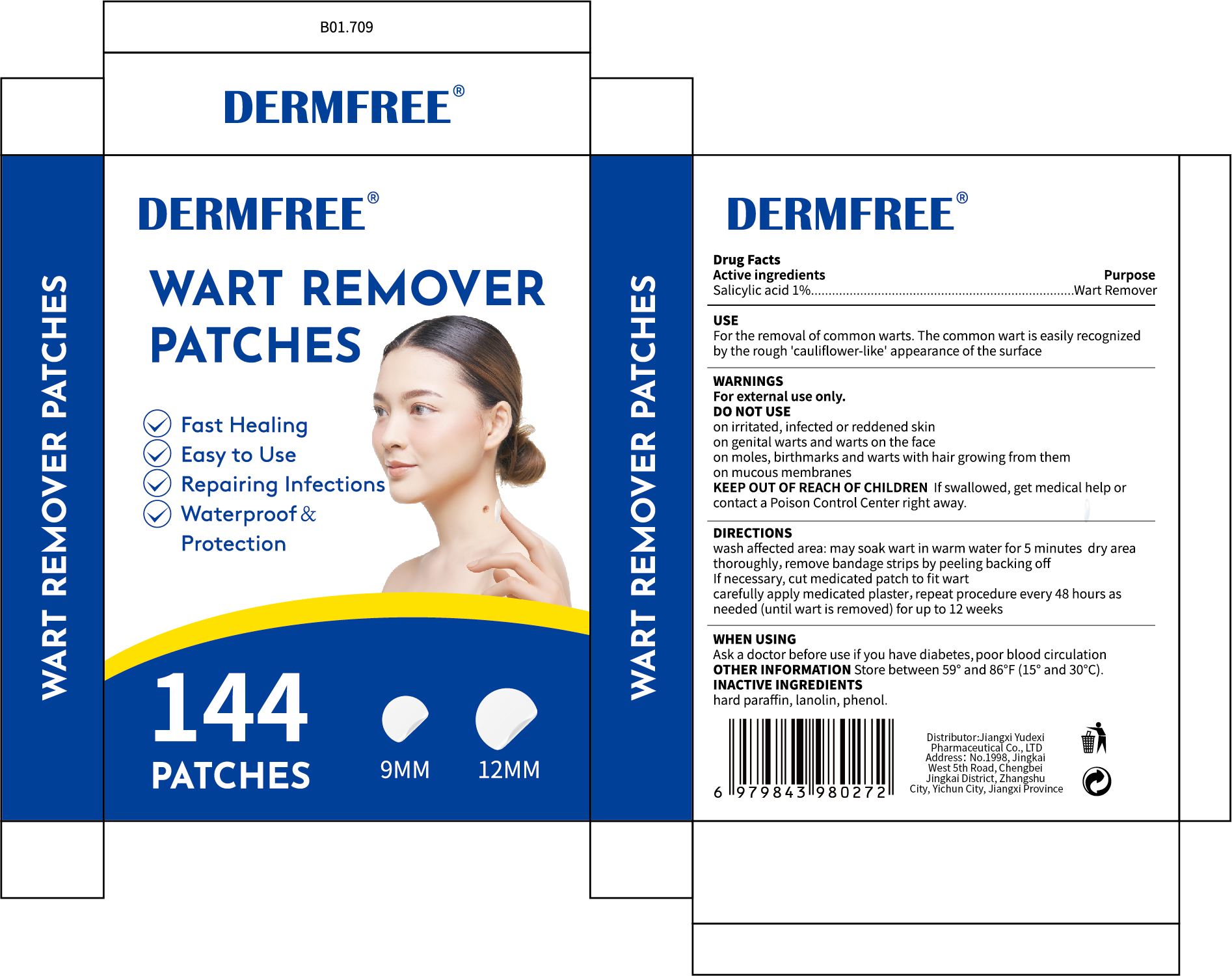 DRUG LABEL: DERMFREE WART REMOVER
NDC: 85248-119 | Form: PATCH
Manufacturer: Jiangxi Yudexi Pharmaceutical Co., LTD
Category: otc | Type: HUMAN OTC DRUG LABEL
Date: 20260208

ACTIVE INGREDIENTS: SALICYLIC ACID 1 g/100 1
INACTIVE INGREDIENTS: PHENOL; LANOLIN; PARAFFIN

85248-119

Active Ingredient

Salicylic acid 1%

Purpose

Wart Remover

Use

For the removal of common warts. The common wart is easily recognized by the rough 'cauliflower-like' appearance of the surface

Warnings

For external use only.

Do not use

On irritated,infected, or reddened skin; on genital warts and warts on the face; on moles, birthmarks, and warts with hair growing from them;on mucous membranes.

When Using

Ask a doctor before use if you have diabetes, poor blood circulation

Stop Use

Ask a doctor before use if you have diabetes, poor blood circulation

Ask Doctor

Ask a doctor before use if you have diabetes, poor blood circulation

Keep Oot Of Reach Of Children

If swallowed, get medical help or contact a Poison Control Center right away.

Directions

wash affected area: may soak wart in warm water for 5 minutes dry area thoroughly,remove bandage strips by peeling backing off.If necessary,cut medicated patch to fit wart carefully apply medicated plaster, repeat procedure every 48 hours as needed (until wart is removed) for up to 12 week

Other information

Store between 59° and 86°F(15°and 30°C).

Inactive ingredients

hard paraffin,lanolin,phenol.